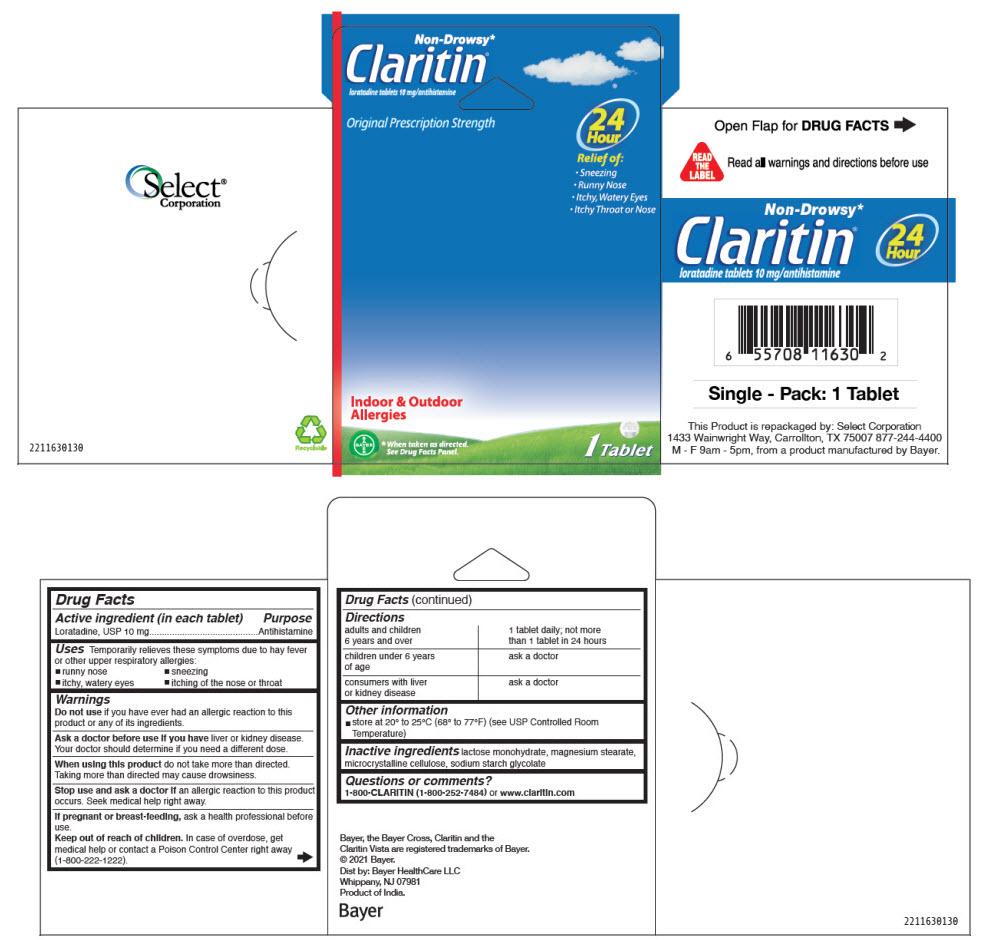 DRUG LABEL: Claritin
NDC: 52904-630 | Form: TABLET
Manufacturer: Select Corporation
Category: otc | Type: HUMAN OTC DRUG LABEL
Date: 20220607

ACTIVE INGREDIENTS: loratadine 10 mg/1 1
INACTIVE INGREDIENTS: lactose monohydrate; STARCH, CORN; magnesium stearate

Claritin®

Drug Facts

Active ingredient (in each tablet)

Loratadine, USP 10 mg

Purpose

Antihistamine

Uses

Temporarily relieves these symptoms due to hay fever or other upper respiratory allergies:

- runny nose
- sneezing
- itchy, watery eyes
- itching of the nose or throat

Warnings

Do not use if you have ever had an allergic reaction to this product or any of its ingredients.

Ask a doctor before use if you have liver or kidney disease. Your doctor should determine if you need a different dose.

When using this product do not take more than directed. Taking more than directed may cause drowsiness.

Stop use and ask a doctor if an allergic reaction to this product occurs. Seek medical help right away.

PREGNANCY OR BREAST FEEDING

If pregnant or breast-feeding, ask a health professional before use.

Keep out of reach of children. In case of overdose, get medical help or contact a Poison Control Center right away (1-800-222-1222).

Directions

adults and children 6 years and over | 1 tablet daily; not more than 1 tablet in 24 hours
children under 6 years of age | ask a doctor
consumers with liver or kidney disease | ask a doctor

Other information

- store at 20° to 25°C (68° to 77°F) (see USP Controlled Room Temperature)

Inactive ingredients

lactose monohydrate, magnesium stearate, microcrystalline cellulose, sodium starch glycolate

Questions or comments?

1-800-CLARITIN (1-800-252-7484) or www.claritin.com

Dist by: Bayer HealthCare LLC
Whippany, NJ 07981

PRINCIPAL DISPLAY PANEL - 10 mg Pouch Blister Pack

Non-Drowsy*
Claritin®
loratadine tablets 10 mg/antihistamine

Original Prescription Strength

24
Hour

Relief of:

- Sneezing
- Runny Nose
- Itchy, Watery Eyes
- Itchy Throat or Nose

Indoor & Outdoor
Allergies

*When taken as directed.
See Drug Facts Panel.

1 Tablet